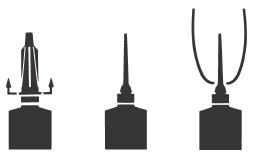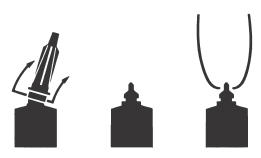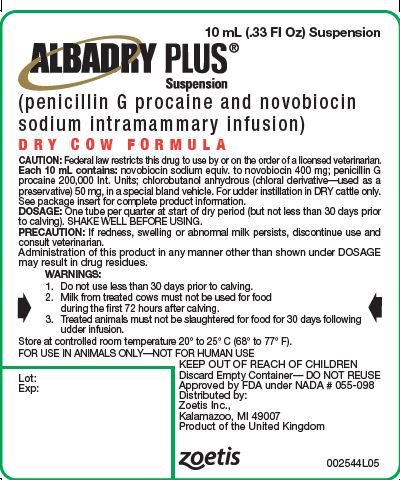 DRUG LABEL: Albadry Plus
NDC: 54771-3139 | Form: INJECTION, SOLUTION
Manufacturer: Zoetis Inc.
Category: animal | Type: PRESCRIPTION ANIMAL DRUG LABEL
Date: 20230608

ACTIVE INGREDIENTS: NOVOBIOCIN SODIUM 400 mg/10 mL; PENICILLIN G PROCAINE 200000 [iU]/10 mL
INACTIVE INGREDIENTS: CHLOROBUTANOL 50 mg/10 mL

Albadry Plus®

VETERINARY INDICATIONS

Albadry Plus®
(penicillin G procaine and novobiocin sodium intramammary infusion)
For the Treatment of Subclinical Mastitis in Dry Cows
For Udder Instillation in Dry Cows Only
FOR USE IN ANIMALS ONLY—NOT FOR HUMAN USE

CAUTION

Federal law restricts this drug to use by or on the order of a licensed veterinarian.

DESCRIPTION

Each 10 mL PLASTET® Disposable Syringe contains:
Novobiocin sodium equiv. to novobiocin | 400 mg
Penicillin G procaine | 200,000 IU
Chlorobutanol anhydrous (chloral derivative—used as a preservative) in a special bland vehicle | 50 mg

Manufactured by a non-sterilizing process.

INDICATIONS FOR USE

ALBADRY PLUS Suspension is indicated for the treatment, in dry cows only, of subclinical mastitis caused by susceptible strains of Staphylococcus aureus and Streptococcus agalactiae.

WARNINGS

1. Do not use less than 30 days prior to calving.

2. Milk from treated cows must not be used for food during the first 72 hours after calving.

3. Treated animals must not be slaughtered for food for 30 days following udder infusion.

PRECAUTION

Administration of this product in any manner other than shown under DOSAGE may result in drug residues.

DOSAGE

Infuse one tube per quarter at start of dry period (but not less than 30 days prior to calving).

Shake Well Before Using

DIRECTIONS FOR USING THE FLEXI-TUBE® SYSTEM

The FLEXI-TUBE is designed to provide the choice of either insertion of the full cannula, as has traditionally been practiced, or insertion of no more than ⅛ inch of the cannula, as recommended by the National Mastitis Council.

- Full Insertion: Remove the blue end cap by pulling straight up as shown. Gently insert the full cannula into the teat canal; carefully infuse the product.
- Partial Insertion: Remove both the blue end cap and the red cannula by pushing sideways as shown. Gently insert the exposed blue tip into the teat canal; carefully infuse the product.

ADMINISTRATION

At the time of drying off, but not less than 30 days prior to calving, milk the udder dry. Wash the teats and udder thoroughly with warm water containing a suitable dairy antiseptic. Dry the teats and udder thoroughly. Infuse each quarter using the following procedure. Using the alcohol pads provided, scrub each teat end clean using a separate pad for each teat. Warm ALBADRY PLUS Suspension to body temperature and shake thoroughly. Choose the desired insertion length (full or partial) and insert tip into teat canal. Instill entire contents into the quarter. Massage the udder after treatment to distribute the ALBADRY PLUS Suspension throughout the quarters. Using a suitable teat dip, dip all teats following treatment.

Discard Empty Container; DO NOT REUSE
KEEP OUT OF REACH OF CHILDREN

STORAGE CONDITIONS

Store at controlled room temperature 20° to 25° C (68° to 77° F).

HOW SUPPLIED

ALBADRY PLUS Suspension is available in unbroken packages of 12–10 mL PLASTET Disposable Syringes with 12 individually wrapped 70% isopropyl alcohol pads and unbroken packages of 144–10 mL PLASTET Disposable Syringes with 144 individually wrapped 70% isopropyl alcohol pads.

Approved by FDA under NADA #055-098

Distributed by:
Zoetis Inc.,
Kalamazoo, MI 49007
Revised: June 2022
002544I10